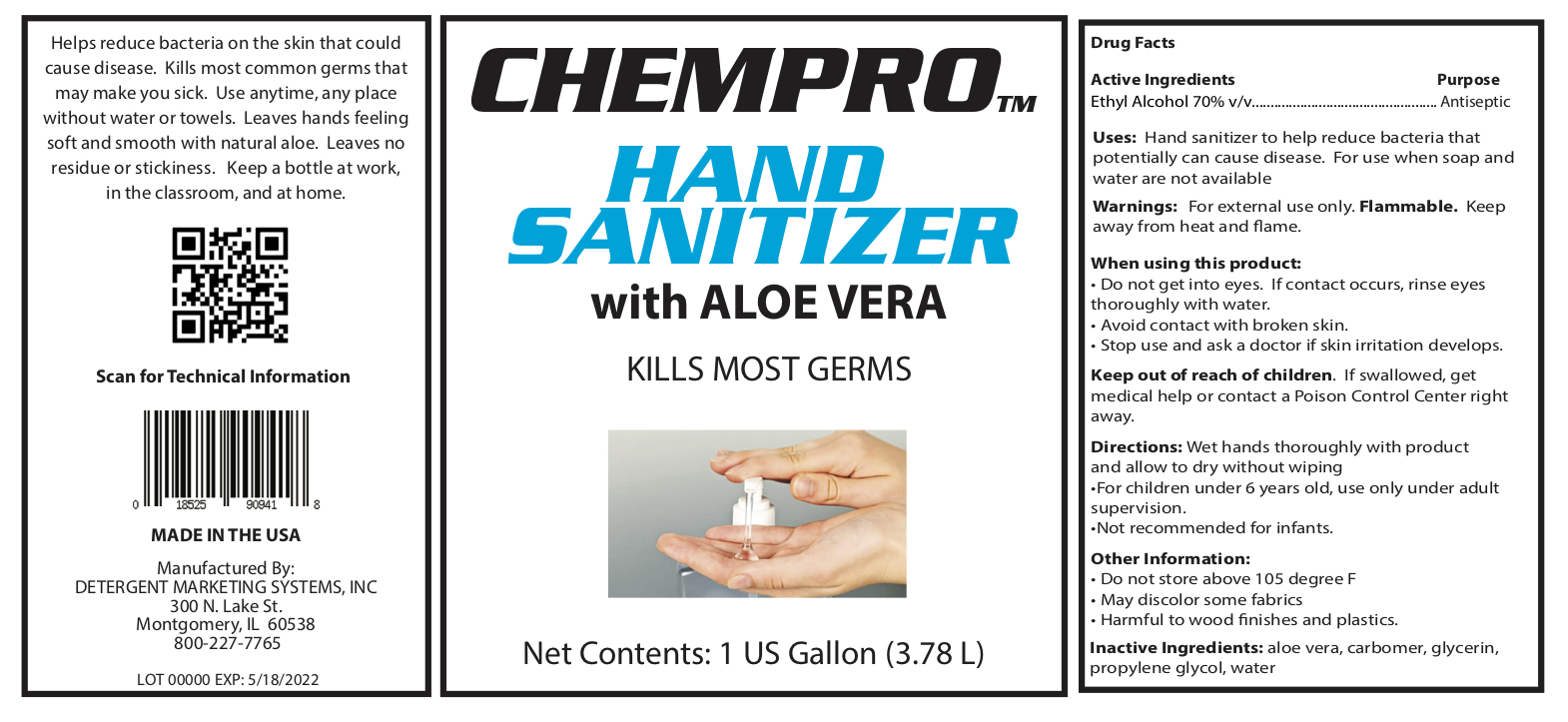 DRUG LABEL: HAND SANITIZER
NDC: 73803-909 | Form: LIQUID
Manufacturer: Detergent Marketing Systems, Inc.
Category: otc | Type: HUMAN OTC DRUG LABEL
Date: 20200518

ACTIVE INGREDIENTS: ALCOHOL 2.646 L/3.78 L
INACTIVE INGREDIENTS: PROPYLENE GLYCOL; CARBOMER 940; WATER; ALOE; GLYCERIN

ACTIVE INGREDIENT

Ethyl Alcohol 70% v/v. Purpose: Antiseptic

PURPOSE

Uses: Hand Sanitizer to help reduce bacteria that potentially can cause disease. For use when soap and water are not available

WARNINGS

Warnings: For external use only. Flammable. Keep away from heat and flame.

When using this product:

- Do not get into eyes. If contact occurs, rinse eyes thoroughly with water.
- Avoid contact with broken skin.
- Stop use and ask a doctor if skin irritation develops.

Keep out of reach of children. If swallowed, get medical help or contact a Poison Control Center right away.

DOSAGE AND ADMINISTRATION

Directions: Wet hands thoroughly with product and allow to dry without wiping

- For children under 6 years old, use only under adult supervision.
- Not recommended for infants.

Other Information:

- Do not store above 105 degree F
- May discolor some fabrics
- Harmful to wood finishes and plastics.

INACTIVE INGREDIENT

Inactive Ingredients: aloe vera, carbomer, glycerin, propylene glycol, water